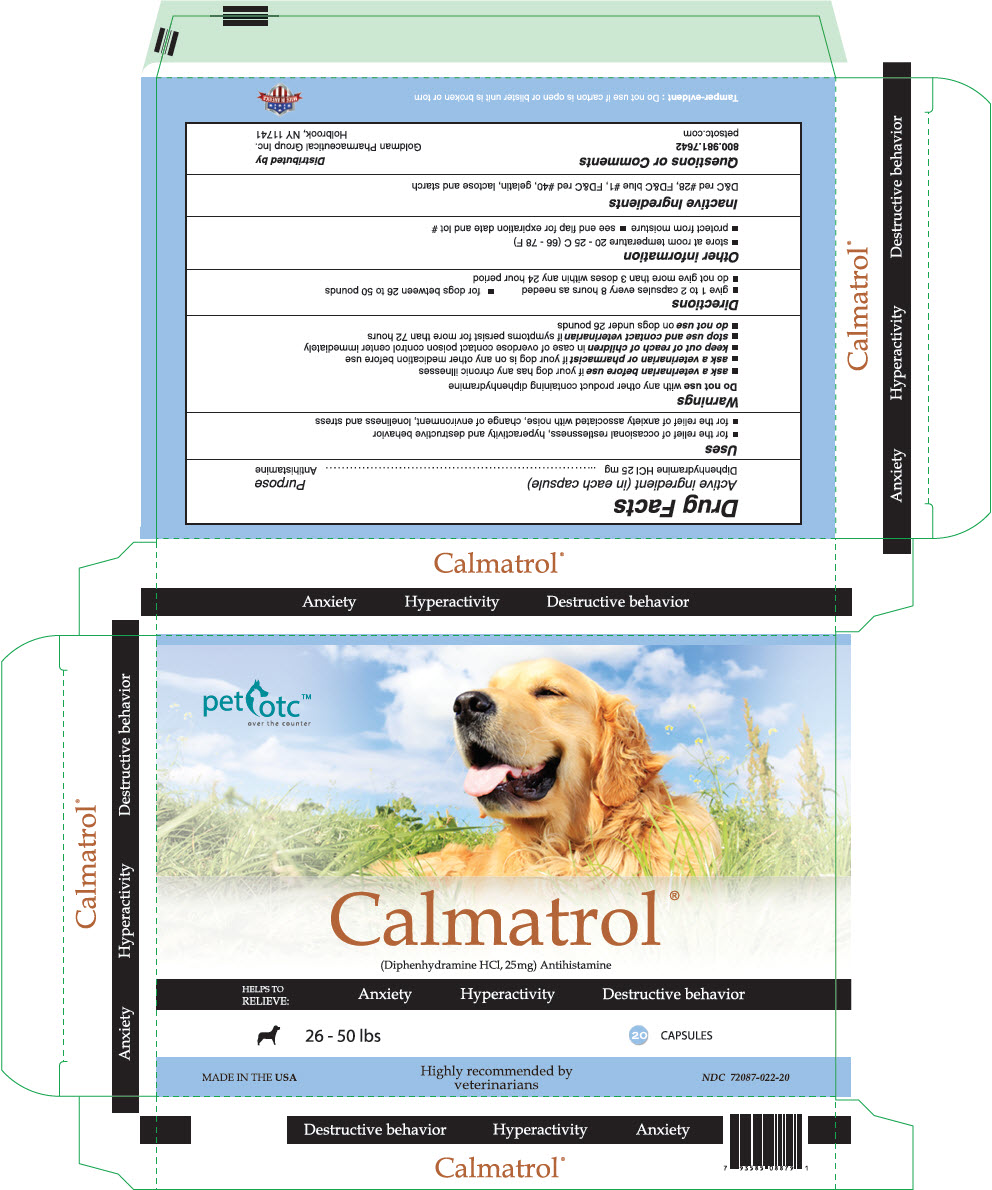 DRUG LABEL: Calmatrol
NDC: 72087-022 | Form: CAPSULE
Manufacturer: Goldman Pharmaceutical Group Inc
Category: animal | Type: OTC ANIMAL DRUG LABEL
Date: 20190220

ACTIVE INGREDIENTS: DIPHENHYDRAMINE HYDROCHLORIDE 25 mg/1 1
INACTIVE INGREDIENTS: BUTYLPARABEN; GELATIN, UNSPECIFIED; MAGNESIUM STEARATE; PROPYLPARABEN; POLYSORBATE 80; STARCH, CORN; METHYLPARABEN

Calmatrol®

Drug Facts

Active ingredient (in each capsule) | Purpose
Diphenhydramine HCl 25 mg | Antihistamine

Uses

- for the relief of occasional restlessness, hyperactivity and destructive behavior
- for the relief of anxiety associated with noise, change of environment, loneliness and stress

Warnings

Do not use with any other product containing diphenhydramine

- ask a veterinarian before use if your dog has any chronic illnesses
- ask a veterinarian or pharmacist if your dog is on any other medication before use
- keep out of reach of children in case of overdose contact poison control center immediately
- stop use and contact veterinarian if symptoms persist for more than 72 hours
- do not use on dogs under 26 pounds

Directions

- give 1 to 2 capsules every 8 hours as needed
- for dogs between 26 to 50 pounds
- do not give more than 3 doses within any 24 hour period

Other information

- store at room temperature 20 - 25 C (66 - 78 F)
- protect from moisture
- see end flap for expiration date and lot #

Inactive Ingredients

D&C red #28, FD&C blue #1, FD&C red #40, gelatin, lactose and starch

Questions or Comments

800.981.7642
petsotc.com

Distributed by
Goldman Pharmaceutical Group Inc.
Holbrook, NY 11741

Tamper-evident : Do not use if carton is open or blister unit is broken or torn

MADE IN AMERICA

PRINCIPAL DISPLAY PANEL - 25 mg Capsule Blister Pack Carton

pet otc™
over the counter

Calmatrol®
(Diphenhydramine HCl, 25mg) Antihistamine

HELPS TO
RELIEVE:
Anxiety
Hyperactivity
Destructive behavior

26 - 50 lbs
20 CAPSULES

MADE IN THE USA

Highly recommended by
veterinarians

NDC 72087-022-20